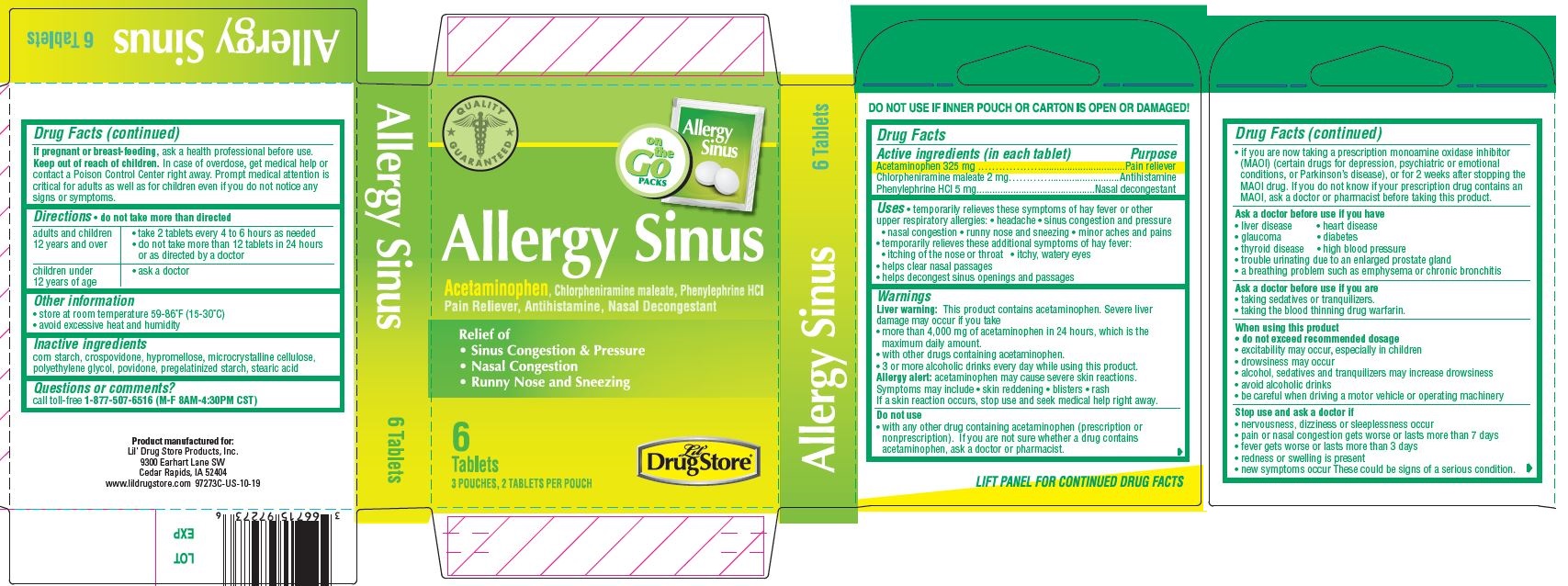 DRUG LABEL: Allergy Sinus, Lil Drug Store
NDC: 66715-9927 | Form: TABLET
Manufacturer: Lil' Drug Store Products, Inc.
Category: otc | Type: HUMAN OTC DRUG LABEL
Date: 20240213

ACTIVE INGREDIENTS: ACETAMINOPHEN 325 mg/1 1; PHENYLEPHRINE HYDROCHLORIDE 5 mg/1 1; CHLORPHENIRAMINE MALEATE 2 mg/1 1
INACTIVE INGREDIENTS: STARCH, CORN; CROSPOVIDONE (15 MPA.S AT 5%); STEARIC ACID; HYPROMELLOSE, UNSPECIFIED; MICROCRYSTALLINE CELLULOSE; POLYETHYLENE GLYCOL, UNSPECIFIED; POVIDONE, UNSPECIFIED

Allergy Sinus, Lil' Drug Store®

Drug Facts

Active ingredients

Active ingredients (in each tablet)

Acetamionophen 325 mg

Chlorpheniramine maleate 2 mg

Phenylephrine Hydrochloride 5 mg

Purpose

Pain reliever

Antihistamine

Nasal decongestant

Uses

- temporarily relieves these symptoms of hay fever or other upper respiratory allergies:
- headache
- sinus congestion and pressure
- nasal congestion
- runny nose and sneezing
- minor aches and pains
- temporarily relieves these additional symptoms of hay fever:
- itching of the nose or throat
- itchy, watery eyes
- helps clear nasal passages
- helps decongest sinus openings and passages

Warnings

Liver warning

Liver warning: This product contains acetaminophen. Severe liver damage may occur if you take

- more than 4,000 mg of acetaminophen in 24 hours, which is the maximum daily amount.
- with other drugs containing acetaminophen.
- 3 or more alcoholic drinks every day while using this product.

Allergy alert

Allergy alert: acetaminophen may cause severe skin reactions.
Symptoms may include

- skin reddening
- blisters
- rash

If a skin reaction occurs, stop use and seek medical help right away.

Do not use

- with any other drug containing acetaminophen (prescription or nonprescription). If you are not sure whether a drug contains acetaminophen, ask a doctor or pharmacist.
- if you are now taking a prescription monoamine oxidase inhibitor (MAOI) (certain drugs for depression, psychiatric or emotional conditions, or Parkinson’s disease), or for 2 weeks after stopping the MAOI drug. If you do not know if your prescription drug contains an MAOI, ask a doctor or pharmacist before taking this product.

Ask a doctor before use if you have

- liver disease
- heart disease
- glaucoma
- diabetes
- thyroid disease
- high blood pressure
- trouble urinating due to an enlarged prostate gland
- a breathing problem such as emphysema or chronic bronchitis

Ask a doctor before use if you are

- taking sedatives or tranquilizers.
- taking the blood thinning drug warfarin.

When using this product

- do not exceed recommended dosage
- excitability may occur, especially in children
- drowsiness may occur
- alcohol, sedatives and tranquilizers may increase drowsiness
- avoid alcoholic drinks
- be careful when driving a motor vehicle or operating machinery

Stop use and ask a doctor if

- nervousness, dizziness or sleeplessness occur
- pain or nasal congestion gets worse or lasts more than 7 days
- fever gets worse or lasts more than 3 days
- redness or swelling is present
- new symptoms occur These could be signs of a serious condition.

If pregnant or breast-feeding, ask a health professional before use.

Keep out of reach of children. In case of overdose, get medical help or contact a Poison Control Center right away. Prompt medical attention is critical for adults as well as for children even if you do not notice any signs or symptoms.

Directions

- do not take more than directed

adults and children 12 years and over | - take 2 tablets every 4 to 6 hours as needed - do not take more than 12 tablets in 24 hours or as directed by a doctor
children under 12 years of age | - ask a doctor

Other information

- store at room temperature 59-86°F (15-30°C)
- avoid excessive heat and humidity

Inactive ingredients

corn starch, crospovidone, hypromellose, microcrystalline cellulose, polyethylene glycol, povidone, pregelatinized starch, stearic acid

Questions or comments?

call toll-free 1-877-507-6516 (M-F 8AM-4:30PM CST)

Allergy Sinus, Lil' Drug Store® - PDP/Package

[caduceus]

on

the

Go

PACKS

Allergy

Sinus [tablets image]

Allergy Sinus

Acetaminophen, Chlorpheniramine maleate, Phenylephrine hydrochloride

Pain Reliever, Antihistamine, Nasal Decongestant

Relief of

- Sinus Congestion & Pressure
- Nasal Congestion
- Runny Nose & Sneezing

6

Tablets

3POUHES, 2 TABLETS PER POUCH

[Lil' Drug Store logo]